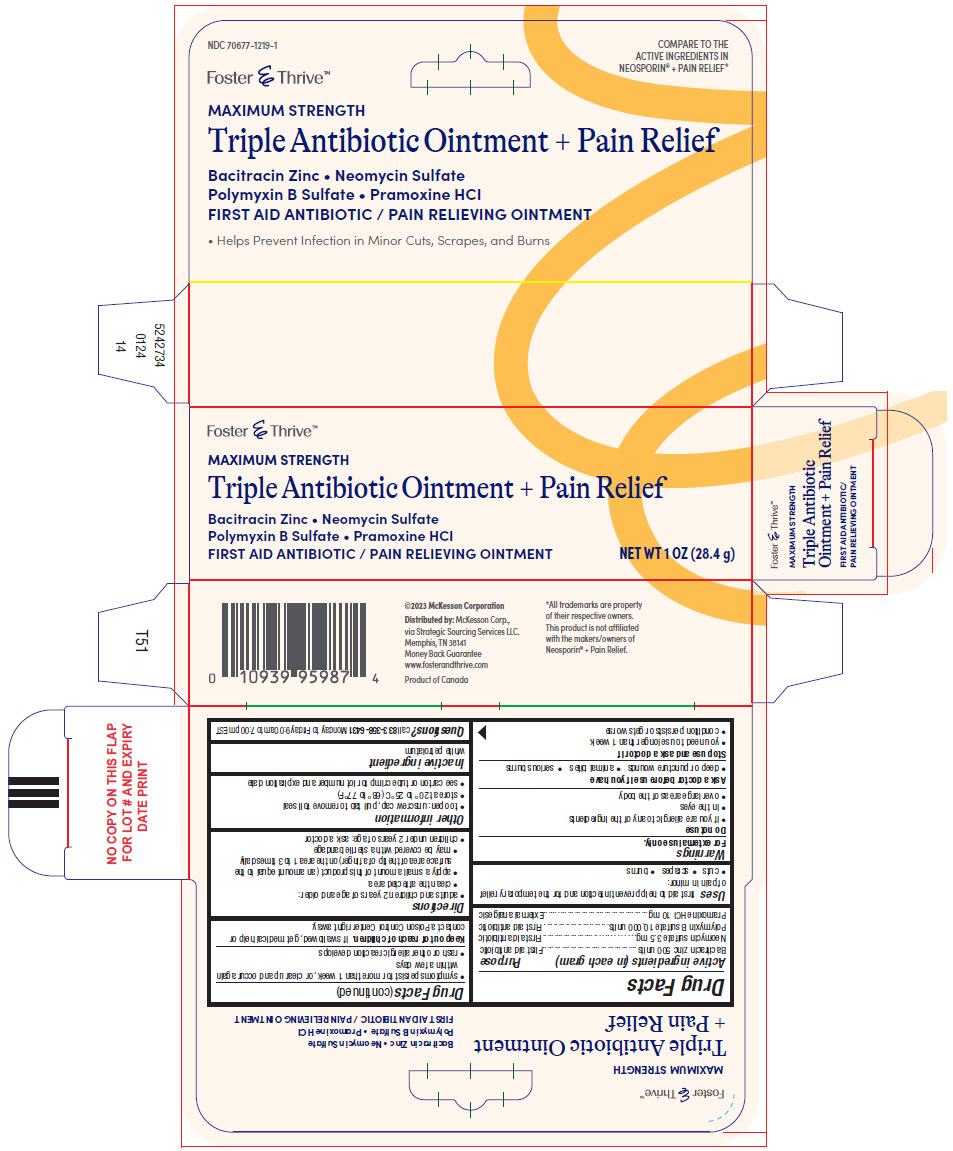 DRUG LABEL: Triple Antibiotic plus Pain Relief
NDC: 70677-1219 | Form: OINTMENT
Manufacturer: STRATEGIC SOURCING SERVICES LLC
Category: otc | Type: HUMAN OTC DRUG LABEL
Date: 20250721

ACTIVE INGREDIENTS: BACITRACIN ZINC 500 [USP'U]/1 g; NEOMYCIN SULFATE 3.5 mg/1 g; POLYMYXIN B SULFATE 10000 [USP'U]/1 g; PRAMOXINE HYDROCHLORIDE 10 mg/1 g
INACTIVE INGREDIENTS: WHITE PETROLATUM

Triple Antibiotic Ointment + Pain Relief

Drug Facts

ACTIVE INGREDIENT

Active ingredients (in each gram) | Purpose
Bacitracin zinc 500 units | First aid antibiotic
Neomycin sulfate 3.5 mg | First aid antibiotic
Polymyxin B sulfate 10,000 units | First aid antibiotic
Pramoxine HCl 10 mg | External analgesic

Uses

first aid to help prevent infection and for the temporary relief of pain in minor:

- cuts
- scrapes
- burns

Warnings

For external use only.

Do not use

- if you are allergic to any of the ingredients
- in the eyes
- over large areas of the body

Ask a doctor before use if you have

- deep or puncture wounds
- animal bites
- serious burns

Stop use and ask a doctor if

- you need to use longer than 1 week
- condition persists or gets worse
- symptoms persist for more than 1 week, or clear up and occur again within a few days
- rash or other allergic reaction develops

Keep out of reach of children.If swallowed, get medical help or contact a Poison Control Center right away.

Directions

- adults and children 2 years of age and older:
  - clean the affected area
  - apply a small amount of this product (an amount equal to the surface area of the tip of a finger) on the area 1 to 3 times daily
  - may be covered with a sterile bandage
- children under 2 years of age: ask a doctor

Other information

- to open: unscrew cap, pull tab to remove foil seal
- store at 20° to 25°C (68° to 77°F)
- see carton or tube crimp for lot number and expiration date

Inactive ingredient

white petrolatum

Questions?

call 833-358-6431Monday to Friday 9:00am to 7:00pm EST

Distributed by:McKesson Corp.,
via Strategic Sourcing Services LLC.
Memphis, TN 38141

PRINCIPAL DISPLAY PANEL - 28.4 g Tube Carton

Foster & Thrive™

MAXIMUM STRENGTH
Triple Antibiotic Ointment + Pain Relief

Bacitracin Zinc • Neomycin Sulfate
Polymyxin B Sulfate • Pramoxine HCl
FIRST AID ANTIBIOTIC / PAIN RELIEVING OINTMENT

NET WT 1 OZ (28.4 g)